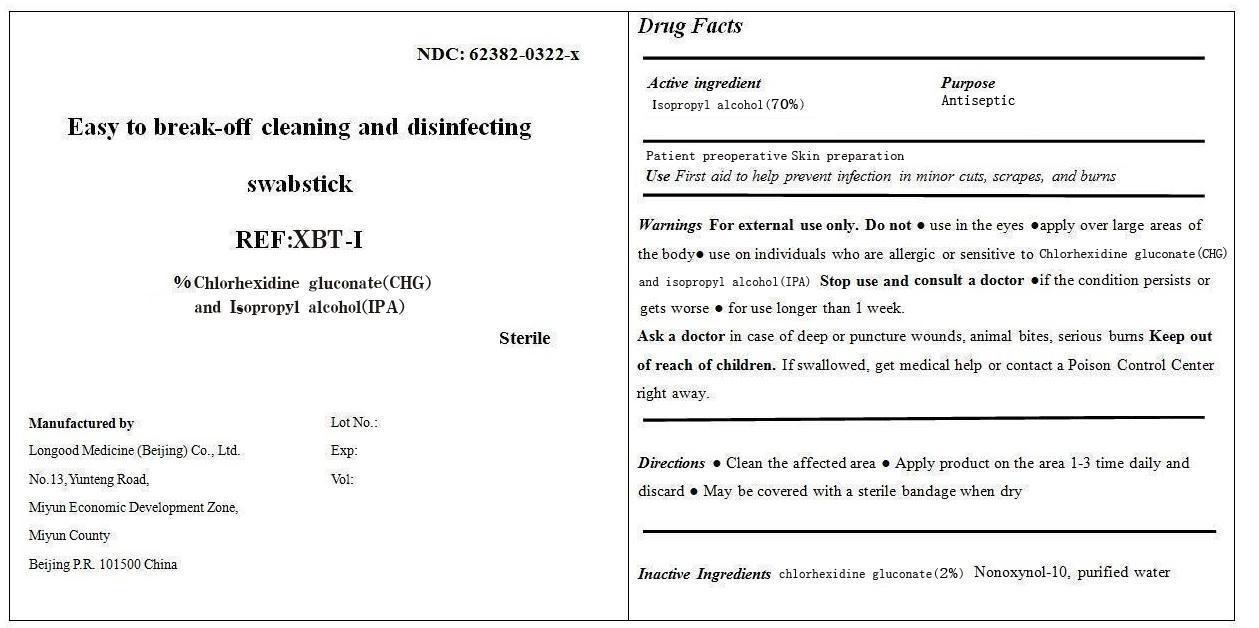 DRUG LABEL: Easy to break-off cleaning and disinfecting swabstick DFB-I
NDC: 62382-0323 | Form: SWAB
Manufacturer: Longood Medicine (Beijing) Co., Ltd.
Category: otc | Type: HUMAN OTC DRUG LABEL
Date: 20150420

ACTIVE INGREDIENTS: ISOPROPYL ALCOHOL 0.7 mL/1 mL
INACTIVE INGREDIENTS: WATER; NONOXYNOL-10; CHLORHEXIDINE GLUCONATE

Drug Fact

Active Ingredient

Isopropyl Alcohol 70%

Chlorhexidine Gluconate 2%

Direction:

- Clean the affected area
- Apply the product to the area 1-3 times daily and discard.
- Maybe coverd with a sterile bandage when dry

Purpose

Antiseptic

Use

First aid to help prevent infection in minor cuts, scrapes, and burns

Warning

For external use only.

Do Not Use

● use in the eyes

●apply over large areas of the body

● use on individuals who are allergic or sensitive to iodine

Stop Use and Consult a Doctor

●if the condition persists or gets worse

● for use longer than 1 week. Ask a doctor in case of deep or puncture wounds, animal bites, serious burns

Ask a doctor in case of deep or puncture wounds, animal bites, serious burns

Keep out of reach of children

If swallowed, get medical help or contact a Poison Control Center right away.

Inactive Ingredient

Chlorhexidine Glutanate, Nonoxynol-10, Purified water